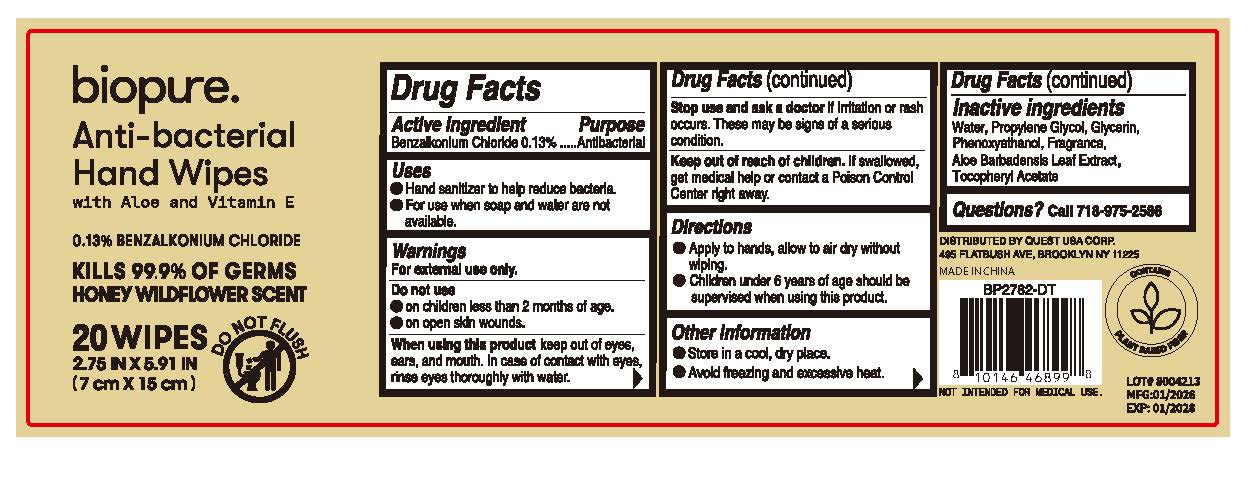 DRUG LABEL: Biopure Anti-bacterial Hand Wipes Honey Wildflower Scent
NDC: 78691-033 | Form: CLOTH
Manufacturer: Quest USA Corp
Category: otc | Type: HUMAN OTC DRUG LABEL
Date: 20260107

ACTIVE INGREDIENTS: BENZALKONIUM CHLORIDE 0.13 g/100 g
INACTIVE INGREDIENTS: ALOE BARBADENSIS LEAF; .ALPHA.-TOCOPHEROL ACETATE, DL-; GLYCERIN; PHENOXYETHANOL; PROPYLENE GLYCOL; WATER

Biopure Anti-bacterial Hand Wipes Honey Wildflower Scent

Active ingredient

Benzalkonium Chloride 0.13%

Purpose

Antibacterial

Uses

- Hand sanitizer to help reduce bacteria.
- For use when soap and water are not available.

Warnings

For external use only.

Do not use

- in children less than 2 months old.
- on open skin wounds.

When using this product

keep out of eyes, ears, and mouth. In case of contact with eyes, rinse eyes thoroughly with water.

Stop use and ask a doctor if

irritation or rash occurs. These may be signs of a serious condition.

Keep out of reach of children.

If swallowed, get medical help or contact a Poison Control Center right away.

Directions

- Apply to hands, allow to air dry without wiping.
- Children under 6 years of age should be supervised when using this product.

Other information

- Store in a cool, dry place.
- Avoid freezing and excessive heat.

Inactive ingredients

Aloe Barbadensis Leaf Extract, Alpha-Tocopherol, Fragrance, Glycerin, Phenoxyethanol, Propylene Glycol, Water

Questions?

call 718-975-2586